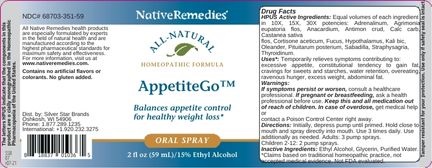 DRUG LABEL: AppetiteGo
NDC: 68703-351 | Form: SPRAY
Manufacturer: Silver Star Brands
Category: homeopathic | Type: HUMAN OTC DRUG LABEL
Date: 20250101

ACTIVE INGREDIENTS: NERIUM OLEANDER LEAF 10 [hp_X]/59 mL; DELPHINIUM STAPHISAGRIA SEED 10 [hp_X]/59 mL; AGRIMONIA EUPATORIA FLOWER 10 [hp_X]/59 mL; SUS SCROFA PITUITARY GLAND, POSTERIOR 10 [hp_X]/59 mL; SCHOENOCAULON OFFICINALE SEED 10 [hp_X]/59 mL; POTASSIUM DICHROMATE 10 [hp_X]/59 mL; THYROID, UNSPECIFIED 10 [hp_X]/59 mL; CORTISONE ACETATE 10 [hp_X]/59 mL; EPINEPHRINE 10 [hp_X]/59 mL; OYSTER SHELL CALCIUM CARBONATE, CRUDE 10 [hp_X]/59 mL; ANTIMONY TRISULFIDE 10 [hp_X]/59 mL; ANACARDIUM OCCIDENTALE FRUIT 10 [hp_X]/59 mL; CASTANEA SATIVA FLOWER 10 [hp_X]/59 mL; FUCUS VESICULOSUS 10 [hp_X]/59 mL; SUS SCROFA HYPOTHALAMUS 10 [hp_X]/59 mL
INACTIVE INGREDIENTS: ALCOHOL; WATER; GLYCERIN

NativeRemedies® AppetiteGo™ Oral Spray

HPUS Active Ingredients: Equal volumes of each ingredient in 10X, 15X, 30X potencies: Adrenalinum, Agrimonia eupatoria flos, Anacardium, Antimon crud, Calc carb, Castanea sativa flos, Cortisone aceticum, Fucus, Hypothalamus, Kali bic, Oleander, Pituitarum posterium, Sabadilla, Staphysagria, Thyroidinum.

Uses*:

Uses*: Temporarily relieves symptoms contributing to: excessive appetite, constitutional tendency to gain fat, cravings for sweets and starches, water retention, overeating, ravenous hunger, excess weight, abdominal fat.

*This statement has not been evaluated by the Food and Drug Administration. This product is not intended to diagnose, treat, cure or prevent any disease.

Warnings

Warnings: If symptoms persist or worsen, consult a healthcare professional. If pregnant or breastfeeding, ask a health professional before use. Keep this and all medication out of reach of children. In case of overdose, get medical help or contact a Poison Control Center right away.

Directions

Directions: Initially, depress pump until primed. Hold close to mouth and spray directly into mouth. Use 3 tiems daily. use additionally as needed. Adults: 3 pump sprays. Children 2-12 : 2 pump sprays.

OTHER SAFETY INFORMATION

Tamper resistant for your protection. Use only if safety seal is intact.

Inactive Ingredients

Inactive Ingredients: Ethyl Alcohol, Glycerin, Purified Water.

KEEP OUT OF REACH OF CHILDREN

Keep this and all medication out of reach of children.

PREGNANCY OR BREAST FEEDING

If pregnant or breastfeeding, ask a health professional before use.

PURPOSE

Balances appetite control for healthy weight loss*

*This statement has not been evaluated by the Food and Drug Administration. This product is not intended to diagnose, treat, cure or prevent any disease.

No changes according to the notes above.